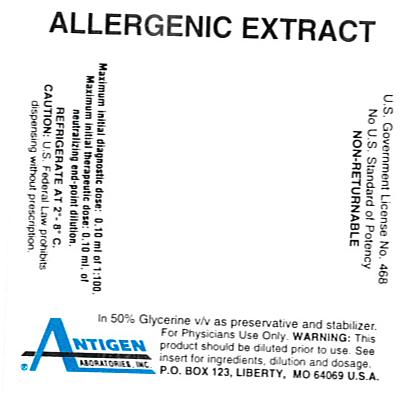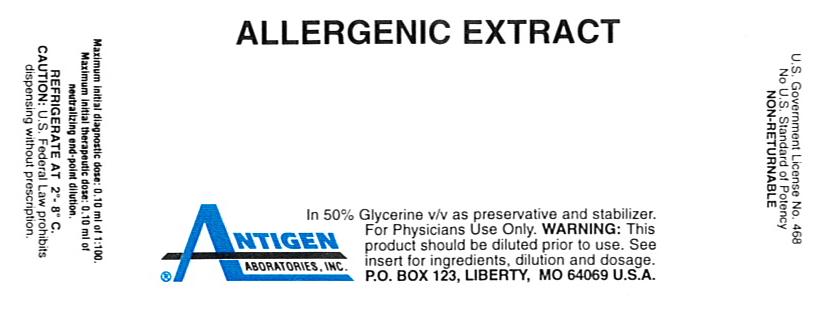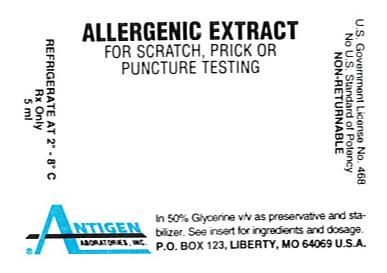 DRUG LABEL: Crab
NDC: 49288-0119 | Form: INJECTION, SOLUTION
Manufacturer: Antigen Laboratories, Inc.
Category: other | Type: NON-STANDARDIZED ALLERGENIC LABEL
Date: 20110722

ACTIVE INGREDIENTS: OPILIO CRAB 0.05 g/1 mL
INACTIVE INGREDIENTS: GLYCERIN 0.525 mL/1 mL; SODIUM CHLORIDE 0.0095 g/1 mL; SODIUM BICARBONATE 0.0024 g/1 mL; WATER

Allergenic Extract

WARNINGS

Allergenic extract is intended for use by, or under the guidance of, physicians who are experienced in the administration of allergenic extracts for diagnosis and/or immunotherapy and the emergency care of anaphylaxis. This extract is not directly interchangeable with other allergenic extracts. The initial dose must be based on skin testing as described in the “DOSAGE AND ADMINISTRATION” section of this insert. Patients switching from other types of extracts to Antigen Laboratories’ allergenic extracts should be started as if they were undergoing treatment for the first time. Patients being switched from one lot of extract to another from the same manufacturer should have the dose reduced by 75%.

Severe systemic reactions may occur with all allergenic extracts. In certain individuals, especially in steroid-dependent/unstable asthmatics, these life-threatening reactions may result in death. Patients should be observed for at least 20 minutes following allergenic extract injections. Treatment and emergency measures, as well as personnel trained in their use, must be available in the event of a life-threatening reaction. Sensitive patients may experience severe anaphylactic reactions resulting in respiratory obstruction, shock, coma and/or death. Report serious adverse events to MedWatch, 5600 Fishers Lane, Rockville, MD 20852-9787, phone 1-800-FDA-1088.

This product should not be injected intravenously. Deep subcutaneous routes have proven to be safe. See the “WARNINGS”, “PRECAUTIONS”, “ADVERSE REACTIONS” and “OVERDOSAGE” sections.

Patients receiving beta-blockers may not be responsive to epinephrine or inhaled bronchodilators. Respiratory obstruction not responding to parenteral or inhaled bronchodilators may require theophylline, oxygen, intubation and the use of life support systems. Parenteral fluid and/or plasma expanders may be utilized for treatment of shock. Adrenocorticosteroids may be administered parenterally or intravenously. Refer to “WARNINGS”, “PRECAUTIONS” and “ADVERSE REACTIONS” sections below.

DESCRIPTION

Antigen Laboratories’ allergenic extracts are manufactured from source material listed on the vial label. Lower concentrations (e.g. 1:50, 1:33, etc.) may be prepared either by dilution from a more concentrated stock or by direct extraction. The extract is a sterile solution containing extractables of source materials obtained from biological collecting and/or processing firms and Antigen Laboratories. All source materials are inspected by Antigen Laboratories’ technical personnel in accordance with 21 CFR 680.1 (b) (1). The route of administration for immunotherapy is subcutaneous. The routes of administration for diagnostic purposes are intradermal or prick-puncture of the skin.

FOR ALLERGENIC EXTRACTS CONTAINING 50% V/V GLYCERINE AS PRESERVATIVE AND STABILIZER:

INACTIVE INGREDIENTS:

Sodium chloride…………………………………………………………….0.95%

Sodium bicarbonate………………………………………………………..0.24%

Glycerine…………………………………………………………………50% (v/v)

Water for Injection…………………………………………………q.s. to volume

Active allergens are described by common and scientific name on the stock concentrate container label or on last page of this circular.

Food allergenic extracts may be manufactured on a weight/volume (w/v) or volume/volume (v/v) basis. Food extracts made from dried raw material are extracted at 2-10% (1:50-1:10 w/v ratio) in extracting fluid containing 50% glycerine. Slurries of juicy fruits or vegetables (prepared with a minimum amount of water for injection) are combined with an equal volume of glycerine for a ration of 1:1 volume/volume (v/v). Sodium chloride and sodium bicarbonate are added to the slurry and glycerine mixture. Fresh egg white extract is prepared by adding one part raw egg white to nine parts of extracting fluid (1:9 v/v).

Antigen E is considered the most important allergen of Short Ragweed pollen and is used for the standardization of Short Ragweed allergenic extracts. Stock mixtures containing Short Ragweed are analyzed for Antigen E content by radial immunodiffusion using Center for Biologics Evaluation and Research (CBER) references and anti-serum. Antigen E content expressed as units of Antigen E per milliliter (U/ml) is printed on container label.

CLINICAL PHARMACOLOGY

Studies indicate allergic individuals produce immunoglobulins of the IgE class in response to exposure to allergens. Subsequent exposure to the allergen results in a combination of allergen with IgE antibody fixed on mast cells or basophil membranes. This cross-linking results in stimulation of mast cell which leads to release and generation of pharmacologically active substances that produce immediate hypersensitivity reaction.^3

The mode of action of immunotherapy with allergenic extracts is still under investigation. Subcutaneous injections of increasing doses of allergenic extract into patients with allergic disease have been shown to result in both humoral and cellular changes including the production of allergen-specific IgG antibodies, the suppression of histamine release from target cells, decrease in circulating levels of antigen specific IgE antibody over long periods of time and suppression of peripheral blood T-lymphocyte cell responses to antigen.^(10, 14, 15)

INDICATIONS AND USAGE

Allergenic extract is used for diagnostic testing and for the treatment (immunotherapy) of patients whose histories indicate that upon natural exposure to the allergen, they experience allergic symptoms. Confirmation is determined by skin testing. Diagnostic use of allergenic extracts usually begins with direct skin testing. This product is not intended for treatment of patients who do not manifest immediate hypersensitivity reactions to the allergenic extract following skin testing.

CONTRAINDICATIONS

Do not administer in the presence of diseases characterized by bleeding diathesis. Individuals with autoimmune disease may be at risk of exacerbating symptoms of the underlying disease, possibly due to routine immunization. Patients who have experienced a recent myocardial infarction may not be tolerant of immunotherapy. Children with nephrotic syndrome probably should not receive injections due to immunization causing exacerbation of nephrotic disease.

WARNINGS

Refer to boxed “WARNINGS”, “PRECAUTIONS”, “ADVERSE REACTIONS” and “OVERDOSAGE” sections for additional information on serious adverse reactions and steps to be taken, if any occur.

Extreme caution is necessary when using diagnostic skin tests or injection treatment in highly sensitive patients who have experienced severe symptoms or anaphylaxis by natural exposure, or during previous skin testing or treatment. IN THESE CASES THE POTENCY FOR SKIN TESTS AND THE ESCALATION OF THE TREATMENT DOSE MUST BE ADJUSTED TO THE PATIENT’S SENSITIVITY AND TOLERANCE.

Benefit versus risk needs to be evaluated in steroid dependent asthmatics, patients with unstable asthma or patients with underlying cardiovascular disease.

Injections should never be given intravenously. A 5/8 inch, 25 gauge needle on a sterile syringe allows deep subcutaneous injection. Withdraw plunger slightly after inserting needle to determine if a blood vessel has been entered.

Proper measurement of dose and caution in making injection will minimize reactions. Adverse reactions to allergenic extracts are usually apparent within 20-30 minutes following injection of immunotherapy.

Extract should be temporarily withheld or dosage reduced in case of any of the following conditions: 1) flu or other infection with fever; 2) exposure to excessive amounts of allergen prior to injection; 3) rhinitis and/or asthma exhibiting severe symptoms; 4) adverse reaction to previous injection until cause of reaction has been evaluated by physician supervising patient’s immunotherapy program.

PRECAUTIONS

General:

Immunotherapy must be given under physician’s supervision. Sterile solutions, vials, syringes, etc. must be used. Aseptic technique must be observed in making dilutions from stock concentrates. The usual precautions in administering allergenic extracts are necessary, refer to boxed WARNINGS and “WARNINGS” section. Sterile syringe and needle must be used for each individual patient to prevent transmission of serum hepatitis, Human Immunodeficiency Virus (HIV) and other infectious agents.

Epinephrine 1:1000 should be available. Refer to “OVERDOSAGE” section for description of treatment for anaphylactic reactions.

Information for Patients:

Patient should remain under observation of a nurse, physician, or personnel trained in emergency measures for at least 20 minutes following immunotherapy injection. Patient must be instructed to report any adverse reactions that occur within 24 hours after injection. Possible adverse reactions include unusual swelling and/or tenderness at injection site, rhinorrhea, sneezing, coughing, wheezing, shortness of breath, nausea, dizziness, or faintness. Immediate medical attention must be sought for reactions that occur during or after leaving physician’s office.

Carcinogenesis, Mutagenesis, Impairment of Fertility:

Long term studies in animals have not been conducted with allergenic extract to determine their potential for carcinogenicity, mutagenicity or impairment of fertility.

Pregnancy Category C:

Animal reproduction studies have not been conducted with allergenic extracts. It is not known whether allergenic extracts cause fetal harm during pregnancy or affect reproductive capacity. A systemic reaction to allergenic extract could cause uterine contractions leading to spontaneous abortion or premature labor. Allergenic extracts should be used during pregnancy only if potential benefit justifies potential risk to fetus.^11

Nursing Mothers:

It is not known whether allergenic extracts are excreted in human milk. Because many drugs are excreted in human milk, caution should be exercised when allergenic extracts are administered to a nursing woman.

Pediatric Use:

Allergenic extracts have been used routinely in children, and no special safety problems or specific hazards have been found. Children can receive the same dose as adults. Discomfort is minimized by dividing the dose in half and administering injection at two different sites.^(16, 17)

Drug Interactions:

Antihistamines. Antihistamines inhibit the wheal and flare reaction. The inhibitory effect of conventional antihistamines varies from 1 day up to 10 days, according to the drug and patient’s sensitivity. Long acting antihistamines (e.g., astemizole) may inhibit the wheal and flare for up to forty days.^(1, 2)

Imipramines, phenothiazines, and tranquilizers. Tricyclic antidepressants exert a potent and sustained decrease of skin reactions to histamine. This effect may last for a few weeks. Tranquilizers and antiemetic agents of the phenothiazine class have H1 antihistaminic activity and can block skin tests.^1

Corticosteroids. Short-term (less than 1 week) administration of corticosteroids at the therapeutic doses used in asthmatic patients does not modify the cutaneous reactivity to histamine, compound 48/80, or allergen. Long-term corticosteroid therapy modifies the skin texture and makes the interpretation of immediate skin tests more difficult.^1

Theophylline. It appears that theophylline need not be stopped prior to skin testing.^1

Beta-Blockers. Patients receiving beta-blockers may not be responsive to epinephrine or inhaled bronchodilators. The following are commonly prescribed beta-blockers: Levatol, Lopressor, Propanolol Intersol, Propanolol HCL, Blocadren, Propanolol, Inderal-LA, Visken, Corgard, Ipran, Tenormin, Timoptic. Ophthalmic beta-blockers: Betaxolol, Levobunolol, Timolol, Timoptic. Chemicals that are beta-blockers and may be components of other drugs: Acebutolol, Atenolol, Esmolol, Metoprolol, Nadolol, Penbutolol, Pindolol, Propanolol, Timolol, Labetalol, Carteolol.^1

Beta-adrenergic agents. Inhaled beta2 agonists in the usual doses used for the treatment of asthma do not usually inhibit allergen-induced skin tests. However, oral terbutaline and parenteral ephedrine were shown to decrease the allergen-induced wheal.^1

Cromolyn. Cromolyn inhaled or injected prior to skin tests with allergens or degranulating agents does not alter skin whealing response.^1

Other drugs. Other drugs have been shown to decrease skin test reactivity. Among them, dopamine is the best-documented compound.^1

Specific Immunotherapy. A decreased skin test reactivity has been observed in patients undergoing specific immunotherapy with pollen extracts, grass pollen allergoids, mites, hymenoptera venoms, or in professional beekeepers who are spontaneously desensitized. Finally, it was shown that specific immunotherapy in patients treated with ragweed pollen extract induced a decreased late-phase reaction.^1

ADVERSE REACTIONS

Adverse reactions include, but are not limited to urticaria; itching; edema of extremities; respiratory wheezing or asthma; dyspnea; cyanosis; tachycardia; lacrimation; marked perspiration; flushing of face, neck or upper chest; mild persistent clearing of throat; hacking cough or persistent sneezing.

1) Local Reactions

A mild burning immediately after injection is expected; this usually subsides in 10-20 seconds. Prolonged pain or pain radiating up arm is usually the result of intramuscular injection, making this injection route undesirable. Subcutaneous injection is the recommended route.

Small amounts of erythema and swelling at the site of injection are common. Reactions should not be considered significant unless they persist for at least 24 hours or exceed 50 mm in diameter.

Larger local reactions are not only uncomfortable, but indicate the possibility of a severe systemic reaction if dosage is increased. In such cases dosage should be reduced to the last level not causing reaction and maintained for two or three treatments before cautiously increasing.

Large, persistent local reactions or minor exacerbations of the patient’s allergic symptoms may be treated by local cold applications and/or use of oral antihistamines.

2) Systemic Reactions

Systemic reactions range from mild exaggeration of patient’s allergic symptoms to anaphylactic reactions.^14 Very sensitive patients may show a rapid response. It cannot be overemphasized that, under certain unpredictable combinations of circumstances, anaphylactic shock is always a possibility. Fatalities are rare but can occur.^5 Other possible systemic reaction symptoms are fainting, pallor, bradycardia, hypotension, angioedema, cough, wheezing, conjunctivitis, rhinitis,and urticaria.^(13, 14)

Careful attention to dosage and administration limit such reactions. Allergenic extracts are highly potent to sensitive individuals and OVERDOSE could result in anaphylactic symptoms. Therefore, it is imperative that physicians administering allergenic extracts understand and prepare for treatment of severe reactions. Refer to “OVERDOSAGE” section.

OVERDOSAGE

Refer to “WARNINGS”, “PRECAUTIONS” and “ADVERSE REACTIONS” sections for signs and symptoms of an overdose.

If a systemic or anaphylactic reaction does occur, apply tourniquet above the site of allergenic extract injection and inject intramuscularly or subcutaneously 0.3 to 0.5 ml of 1:1000 Epinephrine-hydrochloride into the opposite arm or gluteal area. Repeat dose in 5-10 minutes if necessary. Loosen tourniquet briefly at 5 minute intervals to prevent circulatory impairment. Discontinue use of the tourniquet after ½ hour.

The epinephrine HCL 1:1000 dose for infants to 2 years is 0.05 to 0.1 ml; for children 2 to 6 years it is 0.15 ml; for children 6 to 12 years it is 0.2 ml.

Symptoms of progressive anaphylaxis include airway obstruction and/or vascular collapse. After administration of epinephrine, profound shock and vasomotor collapse should be treated with intravenous fluids and possibly vasoactive drugs. Monitor airways for obstruction. Oxygen should be given by mask if indicated.

Antihistamines, H2 antagonist, bronchodilators, steroids and theophylline may be used as indicated after providing adequate epinephrine and circulatory support.^4

Patients who have been taking beta-blockers may be unresponsive to epinephrine. Epinephrine or beta-adrenergic drugs (Alupent) may be ineffective. These drugs should be administered even though a beta-blocker may have been taken. The following treatment will be effective whether or not patient is taking a beta-blocker: Aminophylline IV, slow push or drip, Atrovent (Ipratropium bromide) Inhaler, 3 inhalations repeated, Atropine, 0.4 mg/ml, 0.75 to 1.5 ml IM or IV, Solu-Cortef, 100-200 mg IM or IV, Solu-Medrol, 125 mg IM or IV, Glucagon, 0.5-1 mg IM or IV, Benadryl, 50 mg IM or IV, Cimetidine, 300 mg IM or IV, Oxygen via ambu bag.

DOSAGE AND ADMINISTRATION

Refer to “STORAGE” section for proper storage condition for allergenic extract. Parenteral drug products should be inspected visually for particulate matter and discoloration prior to administration, whenever solution and container permit. Some allergenic extracts naturally precipitate.

Physicians undertaking immunotherapy should be concerned with patient’s degree of sensitivity. The initial dilution of allergenic extract, starting dose, and progression of dosage must be carefully determined on the basis of the patient’s history and results of skin tests. Strongly positive skin tests may be risk factors for systemic reactions. Less aggressive immunotherapy schedules may be indicated for such patients.

Precaution is necessary when using extract mixture for skin testing. The diluting effect of individual components within a mixture may cause false negative reactions. Patients extremely sensitive to a common allergen in several components of a mixture may be more likely to experience a systemic reaction than when skin tested individually for each component.^9

PRICK-PUNCTURE TESTING: To identify highly sensitive individuals and as a safety precaution, it is recommended that a prick-puncture test using a drop of the extract concentrate be performed prior to initiating very dilute intradermal testing. Prick-puncture testing is performed by placing a drop of extract concentrate on the skin and puncturing the skin through the drop with a small needle such as a bifurcated vaccinating needle. The most satisfactory sites on the back for skin testing are from the posterior axillary fold to 2.5 cm from the spinal column, and from the top of the scapula to the lower rib margins. The best areas on the arms are the volar surfaces from the axilla to 2.5 or 5 cm above the wrist, skipping the anticubital space. A positive reaction is approximately 10-15 mm erythema with 2.5 mm wheal. Smaller, less conclusive reactions may be considered positive in conjunction with a definitive history of symptoms on exposure to the allergen. The more sensitive the patient the higher the probability that he/she will have symptoms related to the exposure of the offending allergen. Hence, the importance of a good patient history. Less sensitive individuals can be tested intradermally with an appropriately diluted extract.

A positive control using histamine phosphate identifies patients whose skin may not react due to medications, metabolic or other reasons. A negative control (50% glycerine for prick-puncture testing) would exclude false-positive reactions due to ingredients in diluent or patients who have dermatographism.

SINGLE DILUTION INTRADERMAL TESTING: The surface of the upper and lower arm is the usual location for skin testing. It is important that a new, sterile, disposable syringe and needle be used for each extract tested. Intracutaneous test dilutions, five-fold or ten-fold, may be prepared from stock concentrate using physiologic saline as a diluent. (1) Start testing with the most dilute allergenic extract concentration. (2) A volume of 0.02-0.05 ml should be injected slowly into the superficial skin layers making a small bleb (superficial wheal). (3) For patients without a history of extreme sensitivity, or a negative or weakly reactive prick-puncture test, the initial dilution for skin testing should be a dilution at least 1:12,500 w/v. This initial dilution can be prepared by diluting 1:20 to 1:50 w/v (2%-5%) extracts five-fold to 5^-4 or 1:10 w/v (10%) extracts to 5^-5. See “Serial Dilutions Titration Test Dilutions” chart on the next page. Dilute 1:10 w/v (10%) extracts to 10^-3 if using ten-fold dilutions. (4) Sensitive patients with a positive prick-puncture test require a further dilution to at least 1:312,500 w/v. This dilution can be prepared by diluting 1:20 to 1:50 w/v (2% - 5%) extracts to 5^-6 or 1:10 w/v (10%) extracts to 5^-7 (five-fold dilutions). Ten-fold dilution to 10^-6 of a 1:10 w/v (10%) extract would be a safe starting dilution. Size of reactions are quantitated based on size of wheal and erythema. For interpretation of skin reactions, refer to chart below. If after 20 minutes no skin reaction is observed, continue testing using increasing increments of the concentration until a reaction of 5-10 mm wheal and 11-30 mm erythema is obtained, or a concentration of 5^-2 or 10^-1 has been tested. A negative control, 50% glycerine diluted with diluent to 5^-2 (1:25) or 10^-1 (1:10) dilution and a positive control of histamine phosphate, should be tested and included in interpretation of skin reactions.^(1, 13)

GRADE | mm ERYTHEMA | mm WHEAL
0 | less than 5 | less than 5
± | 5-10 | 5-10
1+ | 11-20 | 5-10
2+ | 21-30 | 5-10
3+ | 31-40 | 10-15 or with pseudopods
4+ | greater than 40 | greater than 15 or with many pseudopods

INTRADERMAL TESTING-SKIN ENDPOINT TITRATION: The allergenic extracts to which the patient is sensitive, the patient’s degree of sensitivity and the dose of allergen to be used in immunotherapy can be determined through the use of intracutaneous skin tests involving progressive five-fold dilutions of allergenic extracts. Intracutaneously inject 0.01 to 0.02 ml of the test allergen to form a 4 mm diameter superficial skin wheal. For patients demonstrating a negative or weakly reactive prick-puncture skin test, an initial screening dilution of 1:12,500 w/v is safe. For patients demonstrating a positive prick-puncture skin test, an initial screening dilution of 1:312,500 w/v is safe. (See “Serial Dilution Titration Test Dilutions” chart below.) When a sequence of five-fold or ten-fold dilutions of an allergen are injected, the endpoint is determined by noting the dilution that first produces a wheal and erythema (15 minutes after injection) that is 2 mm larger than wheals with erythema produced by weaker, non-reacting dilutions (5 mm negative wheal). The endpoint dilution is used as a starting dose concentration for immunotherapy. An endpoint dose of 0.15 ml is a safe initial dose to be followed by escalation to the optimal maximum tolerated dose for each individual.

Injections should never be given intravenously. A 5/8 inch, 25 gauge needle on a sterile syringe will allow deep subcutaneous injection.

IMMUNOTHERAPY: If the first injection of the initial dilution of extract is tolerated without significant local reaction, increasing doses by 5-20% increments of that dilution may be administered. The rate of increase in dosage in the early stages of treatment with highly diluted extracts is usually more rapid than the rate of increase possible with more concentrated extracts. This schedule is intended only as a guide and must be modified according to the reactivity of the individual patient. Needless to say, the physician must proceed cautiously in the treatment of the highly sensitive patient who develops large local or systemic reactions.^6

Some patients may tolerate larger doses of the allergenic extract depending on patient response.^7 Because diluted extract tends to lose activity in storage, the first dose from a more concentrated vial should be the same, or less than, the previous dose.^(8, 12)

Dosages progressively increase according to the tolerance of the patient at intervals of one to seven days until, (1) the patient achieves relief from symptoms, (2) induration at the site of injection is no larger than 50 mm in 36 to 48 hours, (3) a maintenance dose is reached (the largest dose tolerated by the patient that relieves symptoms without undesirable local or systemic reactions). This maintenance dose may be continued at regular intervals perennially. It may be necessary to adjust the progression of dosage downward to avoid local and constitutional reactions.

The usual duration of treatment has not been established. A period of two or three years on immunotherapy constitutes an average minimum course of treatment.

SERIAL DILUTION TITRATION TEST DILUTIONS APPROXIMATE ALLERGENIC EXTRACT CONCENTRATION RESULTING FROM 1:5 DILUTION
Titration Number | Dilution Exponent | Weight / Volume | Allergenic Extract Concentrate
Titration Number | Dilution Exponent | Weight / Volume | 1:50 (2%) | 1:40 (2 1/2%) | 1:33 1/3 (3%) | 1:20 (5%) | 1:10 (10%)
No. 1 | 5^-1 | 1:5 | 1:250 | 1:200 | 1:167 | 1:100 | 1:50
No. 2 | 5^-2 | 1:25 | 1:1,250 | 1:1,000 | 1:835 | 1:500 | 1:250
No. 3 | 5^-3 | 1:125 | 1:6,250 | 1:5,000 | 1:4,175 | 1:2,500 | 1:1,250
No. 4 | 5^-4 | 1:625 | 1:31,250 | 1:25,000 | 1:20,875 | 1:12,500 | 1:6,250
No. 5 | 5^-5 | 1:3,125 | 1:156,250 | 1:125,000 | 1:104,375 | 1:62,500 | 1:31,250
No. 6 | 5^-6 | 1:15,625 | 1:781,250 | 1:625,000 | 1:521,875 | 1:312,500 | 1:156,250
No. 7 | 5^-7 | 1:78,125 | 1:3,906,250 | 1:3,125,000 | 1:2,609,375 | 1:1,562,500 | 1:781,250
No. 8 | 5^-8 | 1:390,625 | 1:19,531,250 | 1:15,625,000 | 1:13,046,875 | 1:7,812,500 | 1:3,906,250
No. 9 | 5^-9 | 1:1,953,125 | 1:97,656,250 | 1:78,125,000 | 1:65,234,375 | 1:39,062,500 | 1:19,531,250
No. 10 | 5^-10 | 1:9,765,625 | 1:488,281,250 | 1:390,625,000 | 1:326,171,875 | 1:195,312,500 | 1:97,656,250
No. 11 | 5^-11 | 1:48,828,125 | 1:2,441,406,250 | 1:1,953,125,000 | 1:1,630,859,375 | 1:976,562,500 | 1:488,281,250
No. 12 | 5^-12 | 1:244,140,625 | 1:12,207,031,250 | 1:9,765,625,000 | 1:8,154,296,875 | 1:4,882,812,500 | 1:2,441,406,250

HOW SUPPLIED

Stock concentrates are available in concentrations of 2-10% or weight/volume (w/v) of 1:50, 1:33, 1:20 or 1:10. Some juicy or liquid foods are available at 1:1 volume/volume (v/v) extraction ratio. Fresh egg white extract is available at 1:9 v/v extraction ratio.

Antigen E content of ragweed mixtures ranges from 46-166 U/ml for Ragweed Mixture (Short/Giant/Western/Southern Ragweed), 47-239 U/ml for Short/Giant/Western Ragweed Mixture, and 106-256 U/ml for Short/Giant Ragweed Mixture. Refer to container label for actual Antigen E content.

Extract (stock concentrate) is supplied in 10, 30 and 50 ml containers. Extracts in 5 ml dropper bottles are available for prick-puncture testing. To insure maximum potency for the entire dating period, all stock concentrates contain 50% glycerine v/v.

STORAGE

Store all stock concentrates and dilutions at 2-8° C. Keep at this temperature during office use. The expiration date of the allergenic extracts is listed on the container label. Dilutions of the allergenic extracts containing less than 50% glycerine are less stable. If loss of potency is suspected, potency can be checked using side by side skin testing with freshly prepared dilutions of equal concentration on individuals with known sensitivity to the allergen.

REFERENCES

1. Bousquet, Jean: “In vivo methods for study of allergy: Skin tests” Third Edition, Allergy Principles and Practice, C.V. Mosby Co., Vol. I, Chap. 19, pp 419-436, 1988.

2. Long, W.F., Taylor, R.J., Wagner, C.J., et al.: Skin test suppression by antihistamines and the development of subsensitivity, J. Allergy Clin. Immunol., pp. 76-113, 1985.

3. Holgate, S.T., Robinson, C., Church, Mike: Mediators of Immediate Hypersensitivity, Third Edition, Allergy Principles and Practice, C.V. Mosby Co., Vol. I and II, pp 135-163, 1988.

4. Wasserman, S., Marquart, D.: Anaphylaxis, Third Edition, Allergy Principles and Practice, C.V. Mosby Co., Vol. 1, Chap. 58, pp. 1365-1376, 1988.

5. Reid, Michael J., Lockey, Richard F., Turkeltaub M.D., Paul C., Platts-Mills, Thomas. “Survey of Fatalities from Skin Testing and Immunotherapy 1985-1989”, Journal of Allergy and Clinical Immunology, Vol. 92, No. 1, pp. 6-15, 1993.

6. Matthews, K., et al: Rhinitis, Asthma and Other Allergic Diseases. NIAID Task Force Report, U.S. Dept. HEW, NIH Publication No. 79-387, Chapter 4, pp. 213-217, May 1979.

7. Ishizaka, K.: Control of IgE Synthesis, Third Edition, Allergy Principles and Practices, Vol. I, Chap. 4, p. 52, edited by Middleton et al.

8. Nelson, H.S.: “The Effect of Preservatives and Dilution on the Deterioration of Russian Thistle (Salsola pestifer), a pollen extract.” The Journal of Allergy and Clinical Immunology, Vol. 63, No. 6, pp. 417-425, June 1979.

9. Seebohm, P.M., et al: Panel on Review of Allergenic Extracts, Final Report, Food and Drug Administration, March 13, 1981, pp. 84-86.

10. Rocklin, R.E., Sheffer, A.L., Grainader, D.K. and Melmon, K.: “Generation of antigen-specific suppressor cells during allergy desensitization”, New England Journal of Medicine, 302, May 29, 1980, pp. 1213-1219.

11. Seebohm, P.M., et al: Panel on Review of Allergenic Extracts, Final Report, Food and Drug Administration, March 13, 1981, pp 9-48.

12. Stevens, E.: Cutaneous Tests, Regulatory Control and Standardization of Allergenic Extracts, First International Paul-Ehrlich Seminar, May 20-22, 1979, Frankfurt, Germany, pp. 133-138.

13. Van Metre, T., Adkinson, N., Amodio, F., Lichtenstein, L., Mardinay, M., Norman, P., Rosenberg, G., Sobotka, A., Valentine, M.: “A Comparative Study of the Effectiveness of the Rinkel Method and the Current Standard Method of Immunology for Ragweed Pollen Hay Fever,“ The Journal of Clinical Allergy and Immunology, Vol. 66, No. 6, p. 511, December 1980.

14. Wasserman, S.: The Mast Cell and the Inflammatory Response. The Mast Cell-its role in Health and disease. Edited by J. Pepys & A.M. Edwards, Proceedings of an International Symposium, Davos, Switzerland, Pitman Medical Publishing Co., 1979, pp. 9-20.

15. Perelmutter, L.: IgE Regulation During Immunotherapy of Allergic Diseases. Annals of Allergy, Vol. 57, August 1986.

16. Bullock, J., Frick, O.: Mite Sensitivity in House Dust Allergic Children, Am. J. Dis. Child., pp. 123-222, 1972.

17. Willoughby, J.W.: Inhalant Allergy Immunotherapy with Standardized and Nonstandardized Allergenic Extracts, American Academy of Otolaryngology-Head and Neck Surgery: Instructional Courses, Vol. 1, Chapter 15, C.V. Mosby Co., St. Louis, Missouri, September 1988.